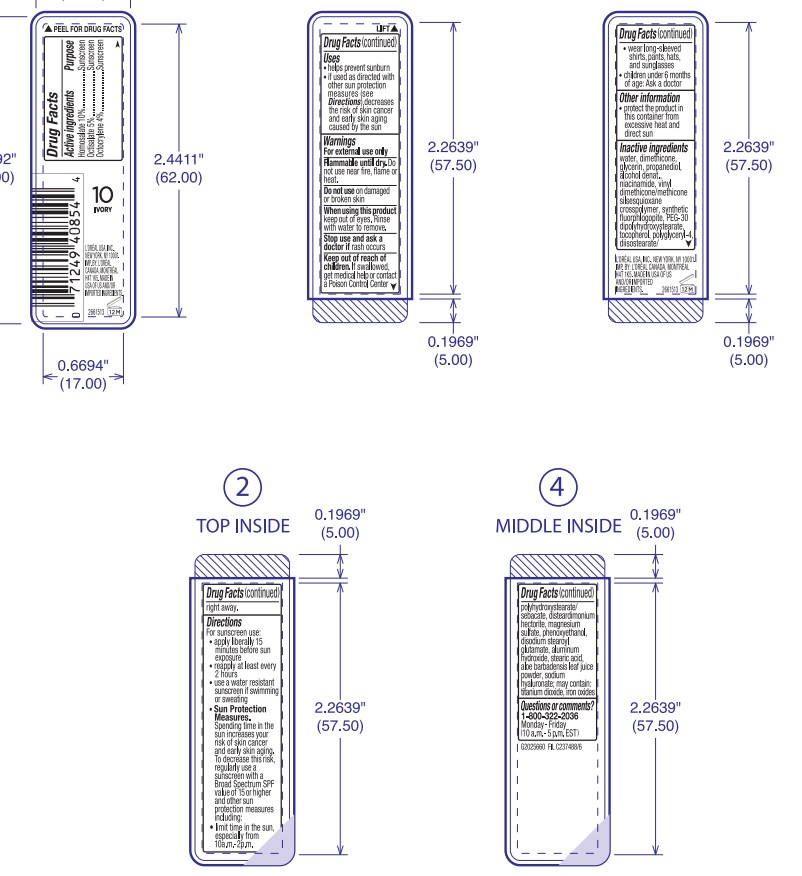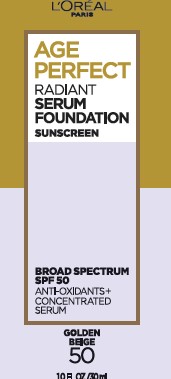 DRUG LABEL: LOreal Paris Age Perfect Radiant Foundation Broad Spectrum SPF 50 Sunscreen with Antioxidants plus Concentrated Serum
NDC: 49967-940 | Form: CREAM
Manufacturer: L'Oreal USA Products Inc
Category: otc | Type: HUMAN OTC DRUG LABEL
Date: 20240628

ACTIVE INGREDIENTS: Homosalate 100 mg/1 mL; Octisalate 50 mg/1 mL; Octocrylene 40 mg/1 mL
INACTIVE INGREDIENTS: WATER; DIMETHICONE; GLYCERIN; PROPANEDIOL; ALCOHOL; NIACINAMIDE; VINYL DIMETHICONE/METHICONE SILSESQUIOXANE CROSSPOLYMER; PEG-30 DIPOLYHYDROXYSTEARATE; TOCOPHEROL; POLYGLYCERYL-4 DIISOSTEARATE/POLYHYDROXYSTEARATE/SEBACATE; DISTEARDIMONIUM HECTORITE; MAGNESIUM SULFATE, UNSPECIFIED FORM; PHENOXYETHANOL; DISODIUM STEAROYL GLUTAMATE; ALUMINUM HYDROXIDE; STEARIC ACID; ALOE VERA LEAF; HYALURONATE SODIUM; TITANIUM DIOXIDE; FERRIC OXIDE RED

Drug Facts

Active ingredients

Homosalate 10%

Octisalate 5%

Octocrylene 4%

Purpose

Sunscreen

Uses

- helps prevent sunburn
- if used as directed with other sun protection measures (see Directions), decreases the risk of skin cancer and early skin aging caused by the sun

Warnings

For external use only

Flammable until dry.

Do not use near fire, flames or heat.

Do not use

on damaged or broken skin

When using this product

keep out of eyes. Rinse with water to remove.

Stop use and ask a doctor if

rash occurs

Keep out of reach of children.

If swallowed, get medical help or contact a Poison Control Center right away.

Directions

For sunscreen use:

- apply liberally 15 minutes before sun exposure
- reapply at least every 2 hours
- use a water resistant sunscren if swimming or sweating
- Sun Protection Measures. Spending time in the sun increases your risk of skin cancer and early skin aging. To decrease this risk, regularly use a sunscreen with a Broad Spectrum SPF value of 15 or higher and other sun protection measures including:
- limit time in the sun, especially from 10 a.m. - 2 p.m.
- wear long-sleeved shirts, pants, hats, and sunglasses
- children under 6 months of age: Ask a doctor

Other information

- protect the product in this container from excessive heat and direct sun

Inactive ingredients

water, dimethicone, glycerin, propanediol, alcohol denat., niacinamide, vinyl dimethicone/methicone silsesquioxane crosspolymer, synthetic fluorphlogopite, PEG-30 dipolyhydroxystearate, tocopherol, polyglyceryl-4 diisostearate/polyhydroxystearate/sebacate, disteardimonium hectorite, magnesium sulfate, phenoxyethanol, disodium stearoyl glutamate, aluminum hydroxide, stearic acid, aloe barbadensis leaf juice powder, sodium hyaluronate; may contain: titanium dioxide, iron oxides

Questions or comments?

1-800-322-2036

Monday - Friday

(10 a.m. - 5 p.m. EST)